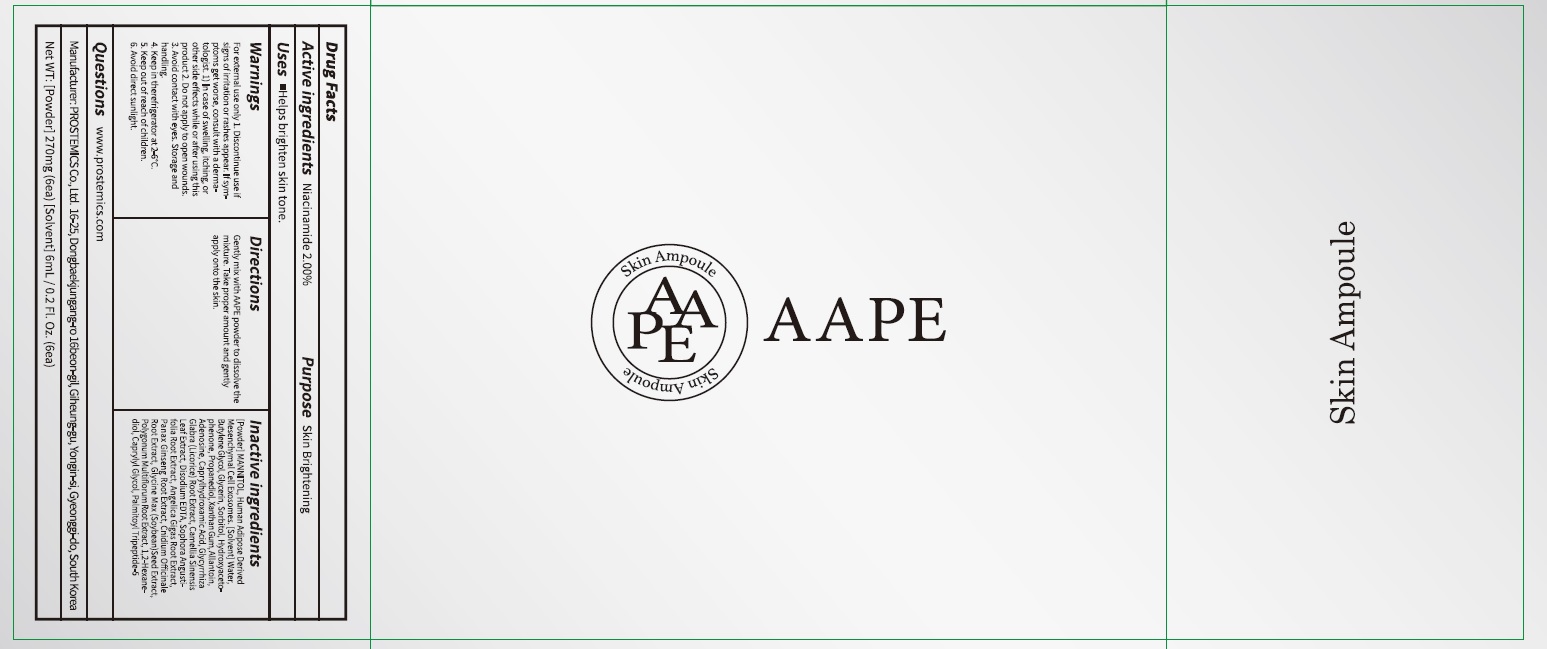 DRUG LABEL: AAPE Skin Ampoule
NDC: 62041-320 | Form: LIQUID
Manufacturer: PROSTEMICS Co., Ltd.
Category: otc | Type: HUMAN OTC DRUG LABEL
Date: 20210528

ACTIVE INGREDIENTS: Niacinamide 2.0 g/100 mL
INACTIVE INGREDIENTS: Water; Butylene Glycol

ACTIVE INGREDIENT

Niacinamide 2.00%

INACTIVE INGREDIENT

[Powder] MANNITOL, Human Adipose Derived Mesenchymal Cell Exosomes.

[Solvent] Water, Butylene Glycol, Glycerin, Sorbitol, Hydroxyacetophenone, Propanediol, Xanthan Gum, Allantoin, Adenosine, Caprylhydroxamic Acid, Glycyrrhiza Glabra (Licorice) Root Extract, Camellia Sinensis Leaf Extract, Disodium EDTA, Sophora Angustifolia Root Extract, Angelica Gigas Root Extract, Panax Ginseng Root Extract, Cnidium Officinale Root Extract, Glycine Max (Soybean) Seed Extract, Polygonum Multiflorum Root Extract, 1,2-Hexanediol, Caprylyl Glycol, Palmitoyl Tripeptide-5

PURPOSE

Skin Brightening

WARNINGS

For external use only
1. Discontinue use if signs of irritation or rashes appear. If symptoms get worse, consult with a dermatologist. 1) In case of swelling, itching, or other side effects while or after using this product
2. Do not apply to open wounds.
3. Avoid contact with eyes.
Storage and handling
4. Keep in the refrigerator at 2-6°C.
5. Keep out of reach of children.
6. Avoid direct sunlight.

KEEP OUT OF REACH OF CHILDREN

Uses

Helps brighten skin tone.

Directions

Gently mix with AAPE powder to dissolve the mixture.
Take proper amount and gently apply onto the skin.

QUESTIONS

www.prostemics.com